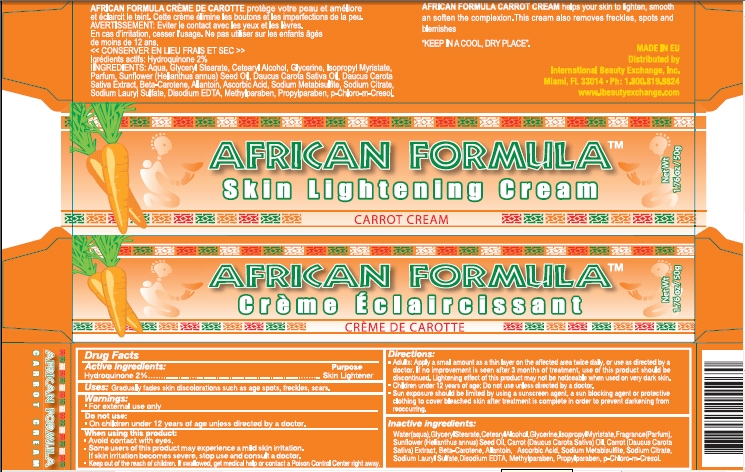 DRUG LABEL: African Formula Carrot
NDC: 66129-105 | Form: CREAM
Manufacturer: International Beauty Exchange
Category: otc | Type: HUMAN OTC DRUG LABEL
Date: 20110311

ACTIVE INGREDIENTS: Hydroquinone 1 g/50 g
INACTIVE INGREDIENTS: WATER; GLYCERYL STEARATE CITRATE; CETOSTEARYL ALCOHOL; GLYCERIN; ISOPROPYL MYRISTATE; SUNFLOWER OIL; CARROT SEED OIL; CARROT; BETA CAROTENE; ALLANTOIN; ASCORBIC ACID; SODIUM METABISULFITE; SODIUM CITRATE; SODIUM LAURYL SULFATE; EDETATE DISODIUM; METHYLPARABEN; PROPYLPARABEN; CHLOROCRESOL

Drug Facts

ACTIVE INGREDIENT

Hydroquinone 2%

WARNINGS

For external use only

DO NOT USE

On children under 12 years of age unless directed by a doctor

WHEN USING

Avoid contact with eyes.

INACTIVE INGREDIENT

Enter section text here

KEEP OUT OF REACH OF CHILDREN

Enter section text here

PURPOSE

Skin Lightener